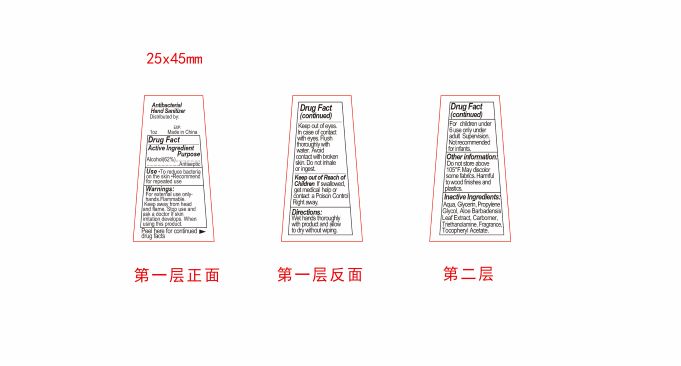 DRUG LABEL: Antibacterial Hand Sanitizer
NDC: 82953-008 | Form: SOLUTION
Manufacturer: Cosmuses Cosmetics (Ningbo) Co., Ltd
Category: otc | Type: HUMAN OTC DRUG LABEL
Date: 20240702

ACTIVE INGREDIENTS: ALCOHOL 62 mL/100 mL
INACTIVE INGREDIENTS: GLYCERIN; TRICLOSAN; WATER; CARBOMER 940; PROPYLENE GLYCOL; ALOE; .ALPHA.-TOCOPHEROL ACETATE; FRAGRANCE FRESH CITRUS FLORAL ORC1501495

Antibacterial Hand Sanitizer

Drug Fact

Active Ingredient(s)

Alcohol 62%

Purpose

Antiseptic

Use

To decrease the bacteria on the skin that could cause disease

Recommended for repeated use

Warnings

For external use only-Hands

Flammable. Keep away from heat and flame

Stop use and ask a doctor if skin irritation develops

WHEN USING

When use this product, keep out of eyes. In case of contact with eyes, flush thoroughly with water. Avoid contact with broken skin. Do not inhale or ingest

Keep out of reach of children. If swallowed, get medical help or contact a Poison Control Center immediately.

Directions

Wet hands thoroughly with products and allow to dry without wiping

For children under 6, use only under adult supervision

Not recommended for infants

Other information

Do not store above 105F

May discolor some fabrics

Harmful to wooden finishes and plastics

Inactive ingredients

Water, glycerin, propylene glycol, aloe barbadensis leaf extract, carbomer, triethanolamine, tocopheryl acetate